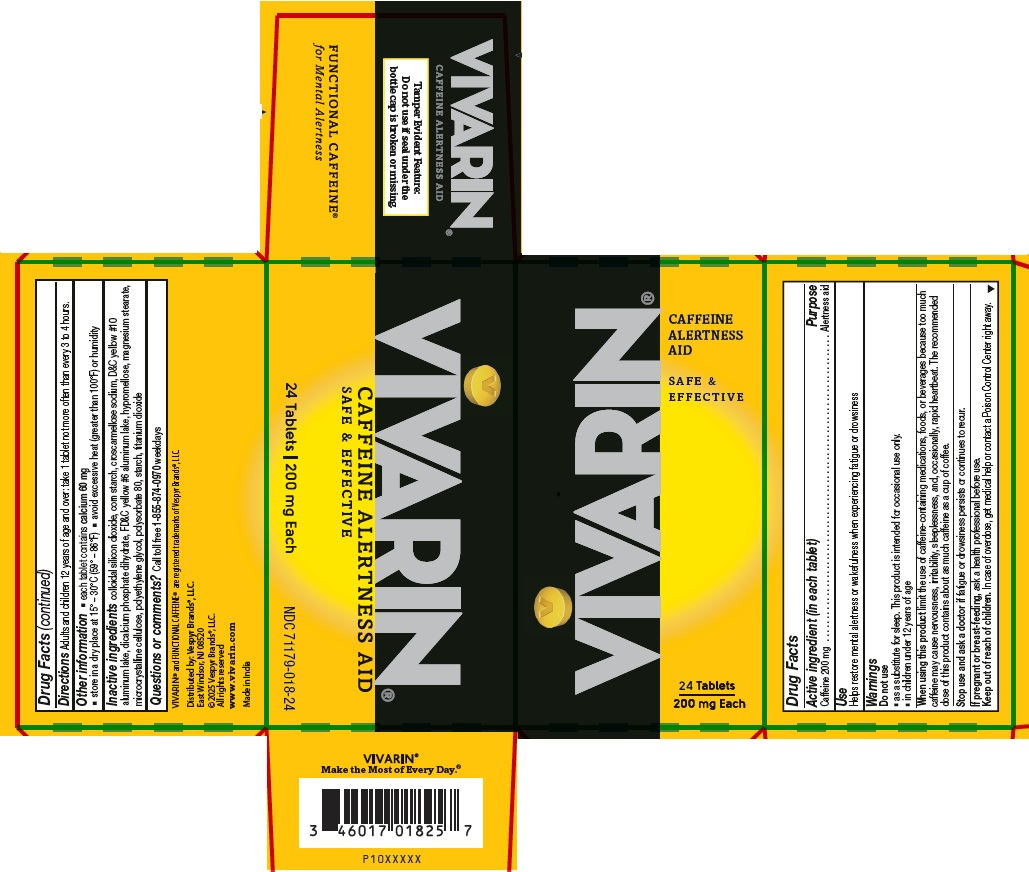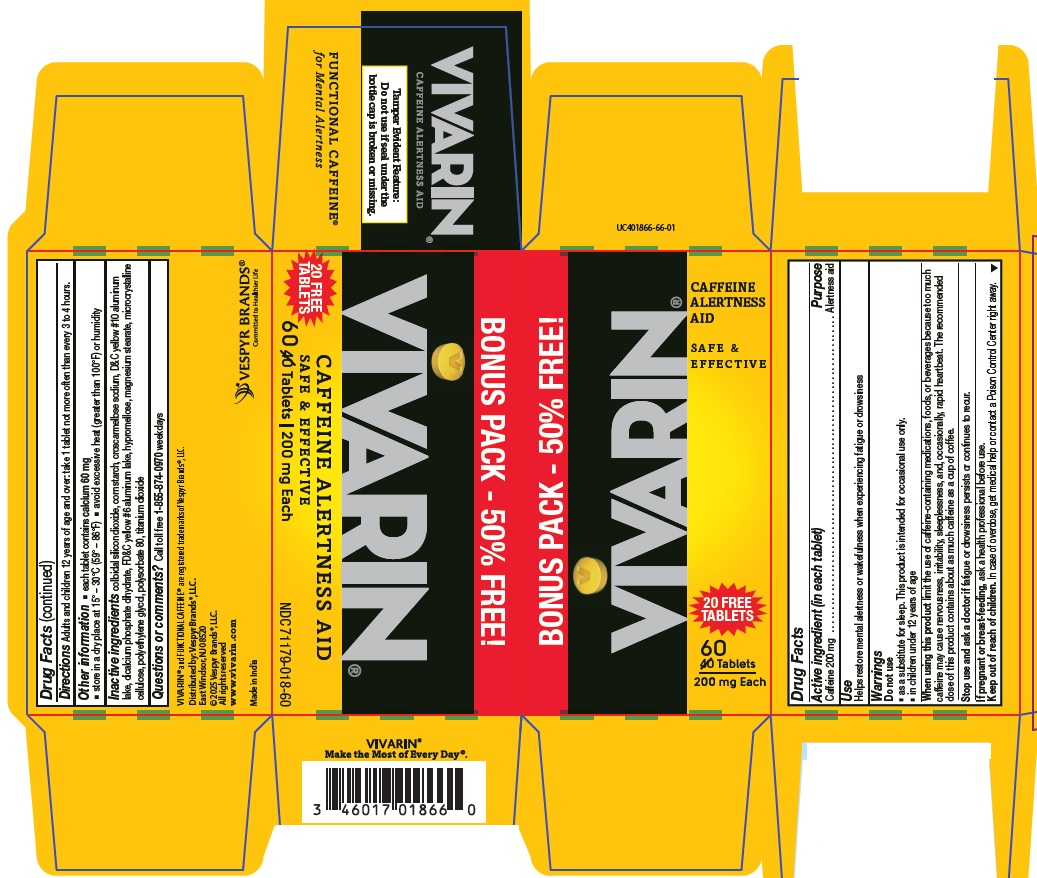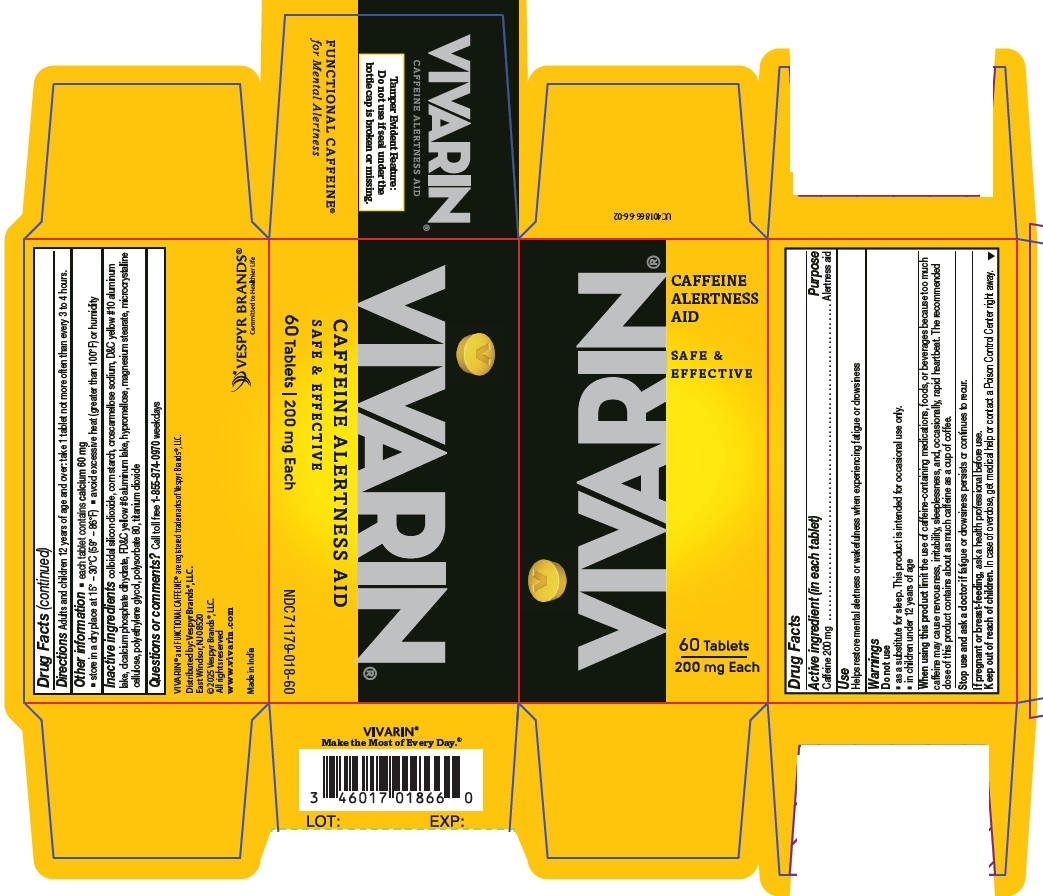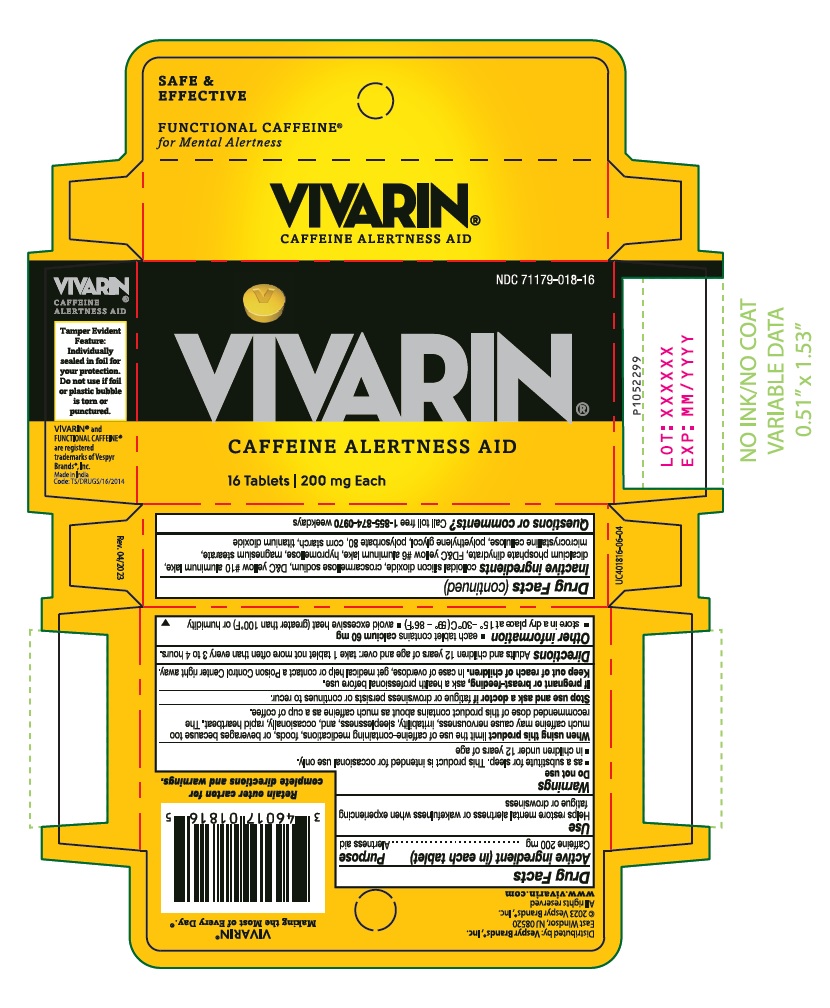 DRUG LABEL: VIVARIN
NDC: 71179-018 | Form: TABLET
Manufacturer: VESPYR BRANDS, INC.
Category: otc | Type: HUMAN OTC DRUG LABEL
Date: 20251001

ACTIVE INGREDIENTS: CAFFEINE 200 mg/1 1
INACTIVE INGREDIENTS: CARNAUBA WAX; SILICON DIOXIDE; CROSCARMELLOSE SODIUM; D&C YELLOW NO. 10 ALUMINUM LAKE; DIBASIC CALCIUM PHOSPHATE DIHYDRATE; MICROCRYSTALLINE CELLULOSE; FD&C YELLOW NO. 6; HYPROMELLOSE, UNSPECIFIED; MAGNESIUM STEARATE; POLYETHYLENE GLYCOL, UNSPECIFIED; POLYSORBATE 80; STARCH, CORN; TITANIUM DIOXIDE

Vivarin

Drug Facts

Active ingredient (in each tablet)

Caffeine 200mg

Purpose

Alertness aid

Use

Helps restore mental alertness or wakefulness when experiencing fatigue or drowsiness

Warnings

Do not use

- as a substitute for sleep. This product is intended for occasional use only.
- in children under 12 years of age

When using this product

limit the use of caffeine-containing medications, foods, or beverages because too much caffeine may cause nervousness, irritability, sleeplessness, and occasionally, rapid heartbeat. The recommended dose of this product contains about as much caffeine as a cup of coffee.

Stop use and ask a doctor if

fatigue or drowsiness persists or continues to recur.

If pregnant or breast-feeding,

ask a health professional before use.

Keep out of reach of children.

In case of overdose, get medical help or contact a Poison Control Center right away.

Directions

Adults and children 12 years of age and over: take 1 tablet not more often than every 3 to 4 hours.

Other information

- each tablet contains calcium 60 mg
- store in a dry place at 15° - 30°C (59° - 86°F)
- avoid excessive heat (greater than 100°F) or humidity

Inactive ingredients

colloidal silicon dioxide, croscarmellose sodium, D&C yellow #10 aluminum lake, dicalcium phosphate dihydrate, FD&C yellow #6 aluminum lake, hypromellose, magnesium stearate, microcrystalline cellulose, polyethylene glycol, polysorbate 80, corn starch, titanium dioxide

Questions or comments?

Call toll-free 1-855-874-0970weekdays
DISTRIBUTED BY:
Vespyr Brands®, Inc.
East Windsor, NJ 08520
Made in India
Code: TS/DRUGS/16/2014

16 Tablets Container Carton

NDC 71179-018-16
V
VIVARIN®
CAFFEINE ALERTNESS AID
16 Tablets | 200 mg Each

24 Tablets Container Carton

VIVARIN

CAFFEINE ALERTNESS AID

SAFE & EFFECTIVE

24 Tablets | 200 mg Each

NDC 71179-018-24

60 Tablets Container Carton

VIVARIN

CAFFEINE ALERTNESS AID

SAFE & EFFECTIVE

60 Tablets | 200 mg Each

NDC 71179-018-24